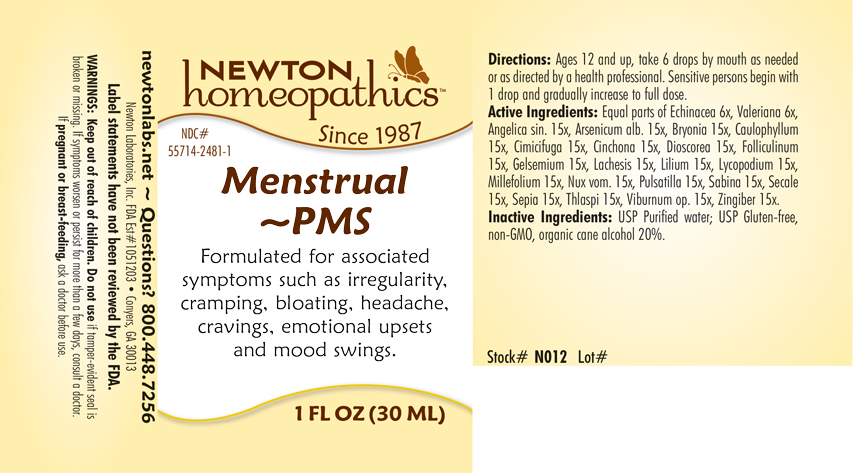 DRUG LABEL: Menstrual - PMS
NDC: 55714-2481 | Form: LIQUID
Manufacturer: Newton Laboratories, Inc.
Category: homeopathic | Type: HUMAN OTC DRUG LABEL
Date: 20250207

ACTIVE INGREDIENTS: ANGELICA SINENSIS ROOT 15 [hp_X]/1 mL; ARSENIC TRIOXIDE 15 [hp_X]/1 mL; BRYONIA ALBA ROOT 15 [hp_X]/1 mL; CAULOPHYLLUM THALICTROIDES ROOT 15 [hp_X]/1 mL; BLACK COHOSH 15 [hp_X]/1 mL; CINCHONA OFFICINALIS BARK 15 [hp_X]/1 mL; DIOSCOREA VILLOSA TUBER 15 [hp_X]/1 mL; ESTRONE 15 [hp_X]/1 mL; GELSEMIUM SEMPERVIRENS ROOT 15 [hp_X]/1 mL; LACHESIS MUTA VENOM 15 [hp_X]/1 mL; LILIUM LANCIFOLIUM WHOLE FLOWERING 15 [hp_X]/1 mL; LYCOPODIUM CLAVATUM SPORE 15 [hp_X]/1 mL; ACHILLEA MILLEFOLIUM 15 [hp_X]/1 mL; STRYCHNOS NUX-VOMICA SEED 15 [hp_X]/1 mL; ANEMONE PULSATILLA 15 [hp_X]/1 mL; JUNIPERUS SABINA LEAFY TWIG 15 [hp_X]/1 mL; CLAVICEPS PURPUREA SCLEROTIUM 15 [hp_X]/1 mL; SEPIA OFFICINALIS JUICE 15 [hp_X]/1 mL; CAPSELLA BURSA-PASTORIS 15 [hp_X]/1 mL; VIBURNUM OPULUS BARK 15 [hp_X]/1 mL; GINGER 15 [hp_X]/1 mL; ECHINACEA, UNSPECIFIED 6 [hp_X]/1 mL; VALERIAN 6 [hp_X]/1 mL
INACTIVE INGREDIENTS: WATER; ALCOHOL

Menstrual 2481L

INDICATIONS & USAGE SECTION

Formulated for associated symptoms such as irregularity, cramping, bloating, headache, cravings, emotional upsets and mood swings.

DOSAGE & ADMINISTRATION SECTION

Directions: Ages 12 and up, take 6 drops by mouth as needed or as directed by a health professional. Sensitive persons begin with 1 drop and gradually increase to full dose.

OTC - ACTIVE INGREDIENT SECTION

Equal parts of Echinacea 6x, Valeriana 6x, Angelica sinensis radix 15x, Arsenicum alb. 15x, Bryonia 15x, Caulophyllum 15x, Cimicifuga 15x, Cinchona 15x, Dioscorea 15x, Folliculinum 15x, Gelsemium 15x, Lachesis 15x, Lilium 15x, Lycopodium 15x, Millefolium 15x, Nux vom. 15x, Pulsatilla 15x, Sabina 15x, Secale 15x, Sepia 15x, Thlaspi 15x, Viburnum op. 15x, Zingiber 15x.

OTC - PURPOSE SECTION

Formulated for associated symptoms such as irregularity, cramping, bloating, headache, cravings, emotional upsets and mood swings.

INACTIVE INGREDIENT SECTION

Inactive Ingredients: USP Purified Water; USP Gluten-free, non-GMO, organic cane alcohol 20%.

QUESTIONS SECTION

newtonlabs.net – Questions? 800.448.7256

Newton Laboratories, Inc. FDA Est # 1051203 - Conyers, GA 30013

WARNINGS SECTION

WARNINGS: Keep out of reach of children. Do not use if tamper-evident seal is broken or missing. If symptoms worsen or persist for more than a few days, consult a doctor. If pregnant or breast-feeding, ask a doctor before use.

OTC - PREGNANCY OR BREAST FEEDING SECTION

If pregnant or breast-feeding, ask a doctor before use.

OTC - KEEP OUT OF REACH OF CHILDREN SECTION

Keep out of reach of children.